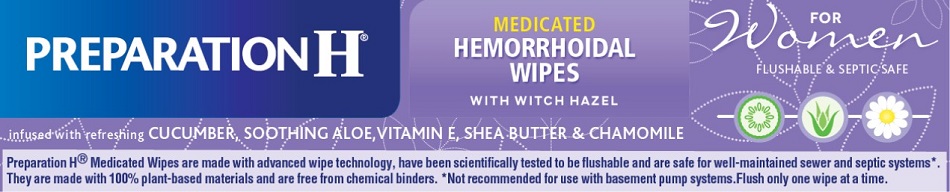 DRUG LABEL: PREPARATION H FOR WOMEN
NDC: 0573-0559 | Form: CLOTH
Manufacturer: Haleon US Holdings LLC
Category: otc | Type: HUMAN OTC DRUG LABEL
Date: 20240301

ACTIVE INGREDIENTS: WITCH HAZEL 2 g/1 1
INACTIVE INGREDIENTS: ALOE VERA LEAF; ANHYDROUS CITRIC ACID; CAPRYL/CAPRAMIDOPROPYL BETAINE; CHAMOMILE; CUCUMBER; DIAZOLIDINYL UREA; DIPROPYLENE GLYCOL; DMDM HYDANTOIN; EDETATE DISODIUM; GLYCERIN; METHYLISOTHIAZOLINONE; METHYLPARABEN; PHENOXYETHANOL; POLYSORBATE 20; PROPYLENE GLYCOL; PROPYLPARABEN; WATER; SODIUM CITRATE, UNSPECIFIED FORM; .ALPHA.-TOCOPHEROL ACETATE

Drug Facts

Active ingredient

Witch hazel 20%

Purpose

Astringent

Uses

- helps relieve the local itching and discomfort associated with hemorrhoids
- temporary relief of irritation and burning
- aids in protecting irritated anorectal areas

Warnings

For external use only

When using this product

- do not exceed the recommended daily dosage unless directed by a doctor
- do not put this product into the rectum by using fingers or any mechanical device or applicator

Stop use and ask a doctor if

- bleeding occurs
- condition worsens or does not improve within 7 days

Keep out of reach of children.If swallowed, get medical help or contact a Poison Control Center right away.

Directions

- open the lid on the top of the wipes pouch
- grab the top wipe at the edge of the center fold and pull out of pouch
- close lid after each use to retain moisture
- adults: unfold wipe and cleanse the area by gently wiping, patting or blotting. If necessary, repeat until all matter is removed from the area.
- use up to 6 times daily or after each bowel movement and before applying topical hemorrhoidal treatments, and then discard
- children under 12 years of age: consult a doctor

Other information

- store at 20-25°C (68-77°F)
- for best results, flush only one or two wipes at a time

Inactive ingredients

aloe barbadensis leaf juice, anhydrous citric acid, capryl/capramidopropyl betaine, chamomilla recutita (matricaria) flower extract, cucumis sativus (cucumber) fruit extract, diazolidinyl urea, dipropylene glycol, DMDM hydantoin, edetate disodium, fragrance, glycerin, methylisothiazolinone, methylparaben, PEG-75 shea butter glycerides, phenoxyethanol, polysorbate 20, propylene glycol, propylparaben, purified water, sodium citrate, vitamin E acetate

Questions or comments?

Call weekdays 9 AM to 5 PM EST at 1-800-99PrepHor 1-800-997-7374

For most recent product information,
visit www.preparationh.com

Other Uses

- for vaginal care– cleanse the area by gently wiping, patting or blotting. Repeat as needed.
- for use as a moist compress– if necessary, first cleanse the area as previously described.

Fold new wipe to desired size and place in contact with tissue for a soothing and cooling effect.

Leave in place for up to 15 minutes and repeat as needed.

PRINCIPAL DISPLAY PANEL

NDC 0573-0559-10

PREPARATION H®
MEDICATED HEMORRHOIDAL WIPES

WITH WITCH HAZEL

FOR Women
FLUSHABLE & SEPTIC SAFE

infused with refreshing
CUCUMBER, SOOTHING ALOE,
VITAMIN E, SHEA BUTTER & CHAMOMILE

PreparationH®Medicated Wipes are made with advanced technology, have been scientifically tested to be flushable and are safe for well-maintained sewer and septic systems*. They are made with 100% plant-based materials and are free from chemical binders. *Not recommended for use with basement pump systems. Flush only one wipe at a time.

PAA113382 Front Carton